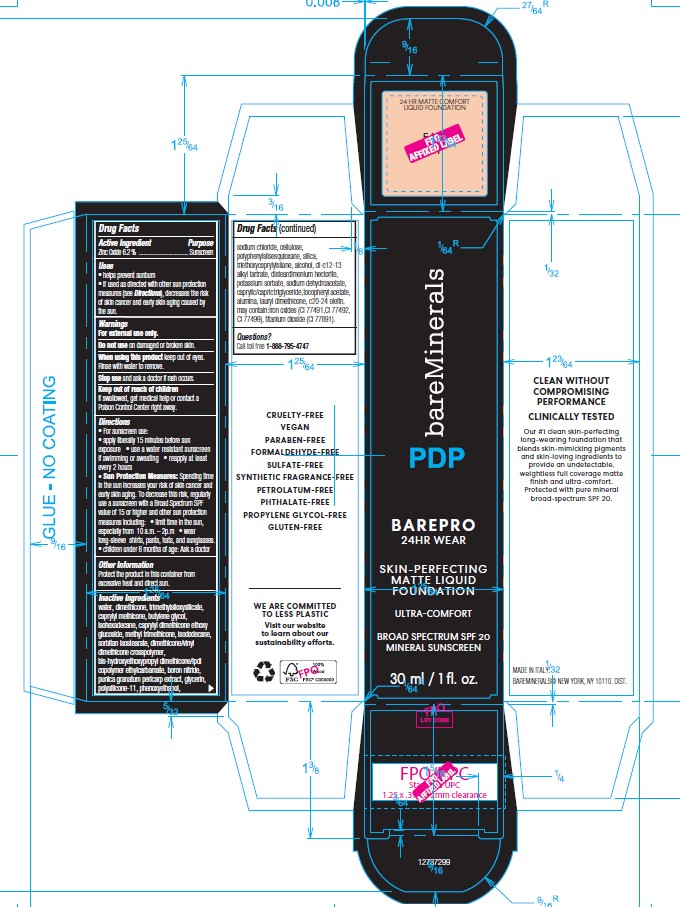 DRUG LABEL: bareMinerals BAREPRO 24HR Wear Skin-Perfecting Matte Liquid Foundation
NDC: 98132-407 | Form: LOTION
Manufacturer: Orveon Global US LLC
Category: otc | Type: HUMAN OTC DRUG LABEL
Date: 20240429

ACTIVE INGREDIENTS: ZINC OXIDE 2.1483 g/34.65 g
INACTIVE INGREDIENTS: C30-38 OLEFIN; TRIMETHYLSILOXYSILICATE (M/Q 0.8-1.0); SODIUM DEHYDROACETATE; FERROSOFERRIC OXIDE; SORBITAN ISOSTEARATE; MEDIUM-CHAIN TRIGLYCERIDES; DISTEARDIMONIUM HECTORITE; WATER; DIMETHICONE; CAPRYLYL TRISILOXANE; BUTYLENE GLYCOL; CAPRYLYL DIMETHICONE ETHOXY GLUCOSIDE; TITANIUM DIOXIDE; FERRIC OXIDE YELLOW; ISOHEXADECANE; ISODODECANE; ALUMINUM OXIDE; METHYL TRIMETHICONE; BORON NITRIDE; DIMETHICONE/VINYL DIMETHICONE CROSSPOLYMER (SOFT PARTICLE); DIMETHICONE/VINYL DIMETHICONE CROSSPOLYMER (HARD PARTICLE); ALCOHOL; SILICON DIOXIDE; POTASSIUM SORBATE; DI-C12-13 ALKYL TARTRATE; TRIETHOXYCAPRYLYLSILANE; POWDERED CELLULOSE; POMEGRANATE FRUIT RIND; SODIUM CHLORIDE; GLYCERIN; PHENOXYETHANOL; FERRIC OXIDE RED; .ALPHA.-TOCOPHEROL ACETATE

Drug Facts

ACTIVE INGREDIENT

Zinc Oxide 6.2%

Active Ingredients Purpose

Zinc Oxide 6.2% Sunscreen

Uses

• helps prevent sunburn
• if used as directed with other sun protection measures (see Directions), decreases the risk of skin cancer and early skin aging caused by the sun.

Warnings

For external use only.

Do not use on damaged or broken skin.

When using this product keep out of eyes. Rinse with water to remove.

Stop use and ask a doctor if rash occurs.

Keep out of reach of children. If swallowed, get medical help or contact a Poison Control Center right away.

Directions

• For sunscreen use:
• apply liberally 15 minutes before sun exposure • use a water resistant sunscreen if swimming or sweating • reapply at least every 2 hours
• Sun Protection Measures: Spending time in the sun increases your risk of skin cancer and early skin aging. To decrease this risk, regularly use a sunscreen with a Broad Spectrum SPF value of 15 or higher and other sun protection measures including: • limit time in the sun, especially from 10 a.m. – 2p.m • wear long-sleeve shirts, pants, hats, and sunglasses.
• children under 6 months of age: Ask a doctor

OTHER SAFETY INFORMATION

Protect the product in this container from excessive heat and direct sun.

Inactive Ingredients

water, dimethicone, trimethylsiloxysilicate, caprylyl methicone, butylene glycol, isohexadecane, caprylyl dimethicone ethoxy glucoside, methyl trimethicone, isododecane, sorbitan isostearate, dimethicone/vinyl dimethicone crosspolymer, bis-hydroxyethoxypropyl dimethicone/ipdi copolymer ethylcarbamate, boron nitride, punica granatum pericarp extract, glycerin, polysilicone-11, phenoxyethanol,sodium chloride, cellulose, polyphenylsilsesquioxane, silica, triethoxycaprylylsilane, alcohol, di-c12-13 alkyl tartrate, disteardimonium hectorite, potassium sorbate, sodium dehydroacetate, caprylic/capric triglyceride, tocopheryl acetate, alumina, lauryl dimethicone, c20-24 olefin. may contain: iron oxides (CI 77491,CI 77492,CI 77499), titanium dioxide (CI 77891).

Questions?

Call toll free 1-888-795-4747